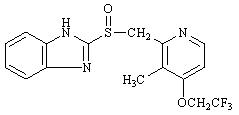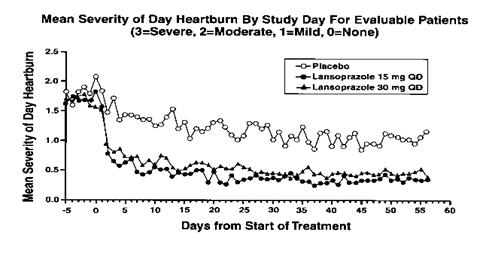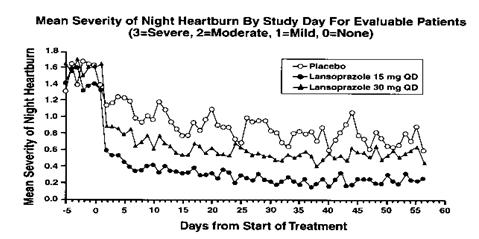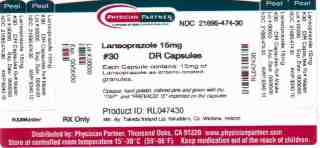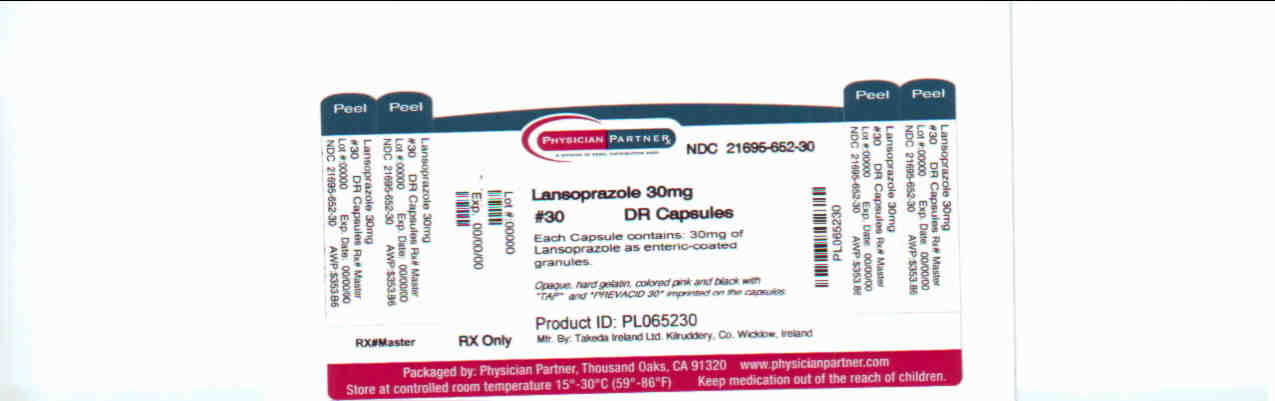 DRUG LABEL: Lansoprazole
NDC: 21695-474 | Form: CAPSULE, DELAYED RELEASE
Manufacturer: Rebel Distributors Corp
Category: prescription | Type: HUMAN PRESCRIPTION DRUG LABEL
Date: 20100930

ACTIVE INGREDIENTS: Lansoprazole 15 mg/1 1
INACTIVE INGREDIENTS: starch, corn; sucrose; hydroxypropyl cellulose, low substituted; magnesium carbonate; talc; polyethylene glycol; titanium dioxide; polysorbate 80; hydroxypropyl cellulose; silicon dioxide; D&C Red No. 28; FD&C Blue No. 1; FD&C Green No. 3; FD&C Red No. 40; methacrylic acid - ethyl acrylate copolymer (1:1) type a

HIGHLIGHTS OF PRESCRIBING INFORMATION

These highlights do not include all the information needed to use Lansoprazole Delayed-Release Capsules safely and effectively. See full prescribing information for:
Lansoprazole Delayed-Release Capsules
For oral administration
Initial U.S. Approval: 1995

RECENT MAJOR CHANGES

Contraindications (4) | April 2008
Warnings and Precautions (5) | April 2008

1 INDICATIONS AND USAGE

Lansoprazole is a proton pump inhibitor (PPI). Refer to DOSAGE and ADMINISTRATION table (below) for indications and usage.

2 DOSAGE AND ADMINISTRATION

Indication | Dose | Frequency
Duodenal Ulcers (1.1, 1.3)
Short-Term Treatment | 15 mg | Once daily for 4 wks
Maintenance of Healed | 15 mg | Once daily
H. pylori Eradication to Reduce Recurrence of Duodenal Ulcer (1.2)
Triple Therapy: Lansoprazole Amoxicillin Clarithromycin | 30 mg 1 gram 500 mg | Twice daily for 10 or 14 days
Dual Therapy: Lansoprazole Amoxicillin | 30 mg 1 gram | Three times daily for 14 days
Benign Gastric Ulcer Short-Term Treatment (1.4) | 30 mg | Once daily up to 8 wks
NSAID-associated Gastric Ulcer (1.6)
Healing Risk Reduction | 30 mg 15 mg | Once daily for 8 wks Once daily up to 12 wks
GERD (1.7)
Short-Term Treatment of Symptomatic GERD | 15 mg | Once daily up to 8 wks
Short-Term Treatment of EE | 30 mg | Once daily up to 8 wks
Pediatric (8.4)
(1 to 11 years of age) Short-Term Treatment of Symptomatic GERD and Short-Term Treatment of EE
≤ 30 kg | 15 mg | Once daily up to 12 wks
> 30 kg | 30 mg | Once daily up to 12 wks
(12 to 17 years of age) Short-Term Treatment of Symptomatic GERD
Nonerosive GERD | 15 mg | Once daily up to 8 wks
EE | 30 mg | Once daily up to 8 wks
Maintenance of Healing of EE (1.8) | 15 mg | Once daily
Pathological Hypersecretory Conditions (i.e., ZES) (1.9) | 60 mg | Once daily

3 DOSAGE FORMS AND STRENGTHS

Capsules: 15 mg and 30 mg. (3)

4 CONTRAINDICATIONS

Contraindicated in patients with known severe hypersensitivity to any component of the lansoprazole delayed-release capsule formulation. (4)

5 WARNINGS AND PRECAUTIONS

Symptomatic response with lansoprazole does not preclude the presence of gastric malignancy. (5)

6 ADVERSE REACTIONS

Most commonly reported adverse reactions (≥1%): diarrhea, abdominal pain, nausea and constipation. (6)

To report SUSPECTED ADVERSE REACTIONS, contact Takeda Pharmaceuticals America Inc. at 1-877-TAKEDA-7 (1-877-825-3327) or FDA at 1-800-FDA-1088 or www.fda.gov/medwatch.

7 DRUG INTERACTIONS

- Do not co-administer with atazanavir. (7)
- May interfere with the absorption of drugs where gastric pH is important for bioavailability (7)
- Concomitant warfarin use may require monitoring for increases in INR and prothrombin time. (7)
- Concomitant tacrolimus use may increase tacrolimus whole blood concentrations. (7)
- Titration of theophylline dosage may be required when concomitant lansoprazole use is started or stopped. (7)

8 USE IN SPECIFIC POPULATIONS

Consider dose adjustment in patients with severe liver impairment (8.7)

FULL PRESCRIBING INFORMATION

1 INDICATIONS AND USAGE

1.1 Short-Term Treatment of Active Duodenal Ulcer

Lansoprazole delayed-release capsules are indicated for short-term treatment (for 4 weeks) for healing and symptom relief of active duodenal ulcer. [See Clinical Studies (14)]

1.2 H. pylori Eradication to Reduce the Risk of Duodenal Ulcer Recurrence

Triple Therapy: lansoprazole/amoxicillin/clarithromycin

Lansoprazole delayed-release capsules in combination with amoxicillin plus clarithromycin as triple therapy are indicated for the treatment of patients with H. pylori infection and duodenal ulcer disease (active or one-year history of a duodenal ulcer) to eradicate H. pylori. Eradication of H. pylori has been shown to reduce the risk of duodenal ulcer recurrence. [See Clinical Studies (14)]

Please refer to the full prescribing information for amoxicillin and clarithromycin.

Dual Therapy: lansoprazole/amoxicillin

Lansoprazole delayed-release capsules in combination with amoxicillin as dual therapy are indicated for the treatment of patients with H. pylori infection and duodenal ulcer disease (active or one-year history of a duodenal ulcer) who are either allergic or intolerant to clarithromycin or in whom resistance to clarithromycin is known or suspected (see the clarithromycin package insert, MICROBIOLOGY section). Eradication of H. pylori has been shown to reduce the risk of duodenal ulcer recurrence. [See Clinical Studies (14)]

Please refer to the full prescribing information for amoxicillin.

1.3 Maintenance of Healed Duodenal Ulcers

Lansoprazole delayed-release capsules are indicated to maintain healing of duodenal ulcers. Controlled studies do not extend beyond 12 months. [See Clinical Studies (14)]

1.4 Short-Term Treatment of Active Benign Gastric Ulcer

Lansoprazole delayed-release capsules are indicated for short-term treatment (up to 8 weeks) for healing and symptom relief of active benign gastric ulcer. [See Clinical Studies (14)]

1.5 Healing of NSAID-Associated Gastric Ulcer

Lansoprazole delayed-release capsules are indicated for the treatment of NSAID-associated gastric ulcer in patients who continue NSAID use. Controlled studies did not extend beyond 8 weeks. [See Clinical Studies (14)]

1.6 Risk Reduction of NSAID-Associated Gastric Ulcer

Lansoprazole delayed-release capsules are indicated for reducing the risk of NSAID-associated gastric ulcers in patients with a history of a documented gastric ulcer who require the use of an NSAID. Controlled studies did not extend beyond 12 weeks. [See Clinical Studies (14)]

1.7 Gastroesophageal Reflux Disease (GERD)

Short-Term Treatment of Symptomatic GERD

Lansoprazole delayed-release capsules are indicated for the treatment of heartburn and other symptoms associated with GERD. [See Clinical Studies (14)]

Short-Term Treatment of Erosive Esophagitis

Lansoprazole delayed-release capsules are indicated for short-term treatment (up to 8 weeks) for healing and symptom relief of all grades of erosive esophagitis. For patients who do not heal with lansoprazole delayed-release capsules for 8 weeks (5 to 10%), it may be helpful to give an additional 8 weeks of treatment. If there is a recurrence of erosive esophagitis an additional 8-week course with lansoprazole delayed-release capsules may be considered. [See Clinical Studies (14)]

1.8 Maintenance of Healing of Erosive Esophagitis (EE)

Lansoprazole delayed-release capsules are indicated to maintain healing of erosive esophagitis. Controlled studies did not extend beyond 12 months. [See Clinical Studies (14)]

1.9 Pathological Hypersecretory Conditions Including Zollinger-Ellison Syndrome

Lansoprazole delayed-release capsules are indicated for the long-term treatment of pathological hypersecretory conditions, including Zollinger-Ellison syndrome. [See Clinical Studies (14)]

2 DOSAGE AND ADMINISTRATION

Lansoprazole delayed-release capsules are available in 15 mg and 30 mg strengths. Directions for use specific to the route and available methods of administration is presented below. Lansoprazole delayed-release capsules should be taken before eating. Lansoprazole delayed-release capsules SHOULD NOT BE CRUSHED OR CHEWED. In the clinical trials, antacids were used concomitantly with lansoprazole delayed-release capsules.

2.1 Recommended Dose

Indication | Recommended Dose | Frequency
Duodenal Ulcers
Short-Term Treatment | 15 mg | Once daily for 4 weeks
Maintenance of Healed | 15 mg | Once daily
H. pylori Eradication to Reduce the Risk of Duodenal Ulcer Recurrence [Please refer to amoxicillin and clarithromycin full prescribing information for CONTRAINDICATIONS and WARNINGS, and for information regarding dosing in elderly and renally-impaired patients.]
Triple Therapy:
Lansoprazole | 30 mg | Twice daily (q12h) for 10 or 14 days
Amoxicillin | 1 gram | Twice daily (q12h) for 10 or 14 days
Clarithromycin | 500 mg | Twice daily (q12h) for 10 or 14 days
Dual Therapy:
Lansoprazole | 30 mg | Three times daily (q8h) for 14 days
Amoxicillin | 1 gram | Three times daily (q8h) for 14 days
Benign Gastric Ulcer Short-Term Treatment | 30 mg | Once daily for up to 8 weeks
NSAID-associated Gastric Ulcer Healing Risk Reduction | 30 mg 15 mg | Once daily for 8 weeks [Controlled studies did not extend beyond indicated duration.] Once daily for up to 12 weeks
Gastroesophageal Reflux Disease (GERD)
Short-Term Treatment of Symptomatic GERD | 15 mg | Once daily for up to 8 weeks
Short -Term Treatment of Erosive Esophagitis | 30 mg | Once daily for up to 8 weeks [For patients who do not heal with lansoprazole for 8 weeks (5 to 10%), it may be helpful to give an additional 8 weeks of treatment. If there is a recurrence of erosive esophagitis, an additional 8 week course of lansoprazole may be considered.]
Pediatric
(1 to 11 years of age)
Short-Term Treatment of Symptomatic GERD and Short-Term Treatment of Erosive Esophagitis
≤ 30 kg | 15 mg | Once daily for up to 12 weeks [The lansoprazole dose was increased (up to 30 mg twice daily) in some pediatric patients after 2 or more weeks of treatment if they remained symptomatic. For pediatric patients unable to swallow an intact capsule please see Administration Options.]
> 30 kg | 30 mg | Once daily for up to 12 weeks
(12 to 17 years of age)
Short-Term Treatment of Symptomatic GERD
Nonerosive GERD | 15 mg | Once daily for up to 8 weeks
Erosive Esophagitis | 30 mg | Once daily for up to 8 weeks
Maintenance of Healing of Erosive Esophagitis | 15 mg | Once daily
Pathological Hypersecretory Conditions Including Zollinger-Ellison Syndrome | 60 mg | Once daily [Varies with individual patient. Recommended adult starting dose is 60 mg once daily. Doses should be adjusted to individual patient needs and should continue for as long as clinically indicated. Dosages up to 90 mg twice daily have been administered. Daily dose of greater than 120 mg should be administered in divided doses. Some patients with Zollinger-Ellison Syndrome have been treated continuously with lansoprazole for more than 4 years.]

2.2 Special Populations

Renal impairment patients and geriatric patients do not require dosage adjustment. However, consider dose adjustment in patients with severe liver impairment. [See Use in Specific Populations (8.5, 8.6 and 8.7)]

2.3 Important Administration Information

Administration Options

Lansoprazole Delayed-Release Capsules - Oral Administration

- Lansoprazole delayed-release capsules should be swallowed whole.
- Alternatively, for patients who have difficulty swallowing capsules, lansoprazole delayed-release capsules can be opened and administered as follows:
  - Open capsule.
  - Sprinkle intact granules on one tablespoon of either applesauce, ENSURE® pudding, cottage cheese, yogurt or strained pears.
  - Swallow immediately.
- Lansoprazole delayed-release capsules may also be emptied into a small volume of either apple juice, orange juice or tomato juice and administered as follows:
  - Open capsule.
  - Sprinkle intact granules into a small volume of either apple juice, orange juice or tomato juice (60 mL – approximately 2 ounces).
  - Mix briefly.
  - Swallow immediately.
  - To ensure complete delivery of the dose, the glass should be rinsed with two or more volumes of juice and the contents swallowed immediately.

USE IN OTHER FOODS AND LIQUIDS HAS NOT BEEN STUDIED CLINICALLY AND IS THEREFORE NOT RECOMMENDED.

Lansoprazole Delayed-Release Capsules - Nasogastric Tube Administration

- For patients who have a nasogastric tube in place, lansoprazole delayed-release capsules can be administered as follows:
  - Open capsule.
  - Mix intact granules into 40 mL of apple juice. DO NOT USE OTHER LIQUIDS.
  - Inject through the nasogastric tube into the stomach.
  - Flush with additional apple juice to clear the tube.

3 DOSAGE FORMS AND STRENGTHS

- 15 mg capsules are opaque, hard gelatin, colored pink and green with the TAP logo and "PREVACID 15" imprinted on the capsule.
- 30 mg capsules are opaque, hard gelatin, colored pink and black with the TAP logo and "PREVACID 30" imprinted on the capsule.

4 CONTRAINDICATIONS

Lansoprazole is contraindicated in patients with known severe hypersensitivity to any component of the formulation of lansoprazole. For information on contraindications for amoxicillin or clarithromycin, refer to their full prescribing information, CONTRAINDICATIONS sections.

5 WARNINGS AND PRECAUTIONS

Symptomatic response to therapy with lansoprazole does not preclude the presence of gastric malignancy. For information on warnings and precautions for amoxicillin or clarithromycin, refer to their full prescribing information, WARNINGS and PRECAUTIONS sections.

6 ADVERSE REACTIONS

6.1 Clinical

Worldwide, over 10,000 patients have been treated with lansoprazole in Phase 2 or Phase 3 clinical trials involving various dosages and durations of treatment. In general, lansoprazole treatment has been well-tolerated in both short-term and long-term trials.

Because clinical trials are conducted under widely varying conditions, adverse reaction rates observed in the clinical trials of a drug cannot be directly compared to rates in the clinical trials of another drug and may not reflect the rates observed in clinical practice.

The following adverse reactions were reported by the treating physician to have a possible or probable relationship to drug in 1% or more of lansoprazole-treated patients and occurred at a greater rate in lansoprazole-treated patients than placebo-treated patients in Table 1.

Table 1: Incidence of Possibly or Probably Treatment-Related Adverse Reactions in Short-Term, Placebo-Controlled Lansoprazole Studies
Body System/Adverse Event | Lansoprazole (N= 2768) % | Placebo (N= 1023) %
Body as a Whole Abdominal Pain | 2.1 | 1.2
Digestive System Constipation Diarrhea Nausea | 1 3.8 1.3 | 0.4 2.3 1.2

Headache was also seen at greater than 1% incidence but was more common on placebo. The incidence of diarrhea was similar between patients who received placebo and patients who received 15 mg and 30 mg of lansoprazole, but higher in the patients who received 60 mg of lansoprazole (2.9%, 1.4%, 4.2%, and 7.4%, respectively).

The most commonly reported possibly or probably treatment-related adverse event during maintenance therapy was diarrhea.

In the risk reduction study of lansoprazole for NSAID-associated gastric ulcers, the incidence of diarrhea for patients treated with lansoprazole, misoprostol, and placebo was 5%, 22%, and 3%, respectively.

Another study for the same indication, where patients took either a COX-2 inhibitor or lansoprazole and naproxen, demonstrated that the safety profile was similar to the prior study. Additional reactions from this study not previously observed in other clinical trials with lansoprazole included contusion, duodenitis, epigastric discomfort, esophageal disorder, fatigue, hunger, hiatal hernia, hoarseness, impaired gastric emptying, metaplasia, and renal impairment.

Additional adverse experiences occurring in less than 1% of patients or subjects who received lansoprazole in domestic trials are shown below:

Body as a Whole – abdomen enlarged, allergic reaction, asthenia, back pain, candidiasis, carcinoma, chest pain (not otherwise specified), chills, edema, fever, flu syndrome, halitosis, infection (not otherwise specified), malaise, neck pain, neck rigidity, pain, pelvic pain

Cardiovascular System - angina, arrhythmia, bradycardia, cerebrovascular accident/cerebral infarction, hypertension/hypotension, migraine, myocardial infarction, palpitations, shock (circulatory failure), syncope, tachycardia, vasodilation

Digestive System – abnormal stools, anorexia, bezoar, cardiospasm, cholelithiasis, colitis, dry mouth, dyspepsia, dysphagia, enteritis, eructation, esophageal stenosis, esophageal ulcer, esophagitis, fecal discoloration, flatulence, gastric nodules/fundic gland polyps, gastritis, gastroenteritis, gastrointestinal anomaly, gastrointestinal disorder, gastrointestinal hemorrhage, glossitis, gum hemorrhage, hematemesis, increased appetite, increased salivation, melena, mouth ulceration, nausea and vomiting, nausea and vomiting and diarrhea, gastrointestinal moniliasis, rectal disorder, rectal hemorrhage, stomatitis, tenesmus, thirst, tongue disorder, ulcerative colitis, ulcerative stomatitis

Endocrine System - diabetes mellitus, goiter, hypothyroidism

Hemic and Lymphatic System - anemia, hemolysis, lymphadenopathy

Metabolic and Nutritional Disorders - avitaminosis, gout, dehydration, hyperglycemia/hypoglycemia, peripheral edema, weight gain/loss

Musculoskeletal System - arthralgia, arthritis, bone disorder, joint disorder, leg cramps, musculoskeletal pain, myalgia, myasthenia, ptosis, synovitis

Nervous System – abnormal dreams, agitation, amnesia, anxiety, apathy, confusion, convulsion, dementia, depersonalization, depression, diplopia, dizziness, emotional lability, hallucinations, hemiplegia, hostility aggravated, hyperkinesia, hypertonia, hypesthesia, insomnia, libido decreased/increased, nervousness, neurosis, paresthesia, sleep disorder, somnolence, thinking abnormality, tremor, vertigo

Respiratory System - asthma, bronchitis, cough increased, dyspnea, epistaxis, hemoptysis, hiccup, laryngeal neoplasia, lung fibrosis, pharyngitis, pleural disorder, pneumonia, respiratory disorder, upper respiratory inflammation/infection, rhinitis, sinusitis, stridor

Skin and Appendages - acne, alopecia, contact dermatitis, dry skin, fixed eruption, hair disorder, maculopapular rash, nail disorder, pruritus, rash, skin carcinoma, skin disorder, sweating, urticaria

Special Senses – abnormal vision, amblyopia, blepharitis, blurred vision, cataract, conjunctivitis, deafness, dry eyes, ear/eye disorder, eye pain, glaucoma, otitis media, parosmia, photophobia, retinal degeneration/disorder, taste loss, taste perversion, tinnitus, visual field defect

Urogenital System - abnormal menses, breast enlargement, breast pain, breast tenderness, dysmenorrhea, dysuria, gynecomastia, impotence, kidney calculus, kidney pain, leukorrhea, menorrhagia, menstrual disorder, penis disorder, polyuria, testis disorder, urethral pain, urinary frequency, urinary retention, urinary tract infection, urinary urgency, urination impaired, vaginitis.

6.2 Postmarketing Experience

Additional adverse experiences have been reported since lansoprazole delayed-release capsules have been marketed. The majority of these cases are foreign-sourced and a relationship to lansoprazole delayed-release capsules have not been established. Because these reactions were reported voluntarily from a population of unknown size, estimates of frequency cannot be made. These events are listed below by COSTART body system.

Body as a Whole – anaphylactic/anaphylactoid reactions; Digestive System - hepatotoxicity, pancreatitis, vomiting; Hemic and Lymphatic System - agranulocytosis, aplastic anemia, hemolytic anemia, leukopenia, neutropenia, pancytopenia, thrombocytopenia, and thrombotic thrombocytopenic purpura; Musculoskeletal System - myositis; Skin and Appendages – severe dermatologic reactions including erythema multiforme, Stevens-Johnson syndrome, toxic epidermal necrolysis (some fatal); Special Senses - speech disorder; Urogenital System – interstitial nephritis, urinary retention.

6.3 Combination Therapy with Amoxicillin and Clarithromycin

In clinical trials using combination therapy with lansoprazole plus amoxicillin and clarithromycin, and lansoprazole plus amoxicillin, no adverse reactions peculiar to these drug combinations were observed. Adverse reactions that have occurred have been limited to those that had been previously reported with lansoprazole, amoxicillin, or clarithromycin.

Triple Therapy: lansoprazole/amoxicillin/clarithromycin

The most frequently reported adverse reactions for patients who received triple therapy for 14 days were diarrhea (7%), headache (6%), and taste perversion (5%). There were no statistically significant differences in the frequency of reported adverse reactions between the 10- and 14-day triple therapy regimens. No treatment-emergent adverse reactions were observed at significantly higher rates with triple therapy than with any dual therapy regimen.

Dual Therapy: lansoprazole/amoxicillin

The most frequently reported adverse reactions for patients who received lansoprazole three times daily plus amoxicillin three times daily dual therapy were diarrhea (8%) and headache (7%). No treatment-emergent adverse reactions were observed at significantly higher rates with lansoprazole three times daily plus amoxicillin three times daily dual therapy than with lansoprazole alone.

For information on adverse reactions with amoxicillin or clarithromycin, refer to their full prescribing information, ADVERSE REACTIONS sections.

6.4 Laboratory Values

The following changes in laboratory parameters in patients who received lansoprazole were reported as adverse reactions:

Abnormal liver function tests, increased SGOT (AST), increased SGPT (ALT), increased creatinine, increased alkaline phosphatase, increased globulins, increased GGTP, increased/decreased/abnormal WBC, abnormal AG ratio, abnormal RBC, bilirubinemia, blood potassium increased, blood urea increased, crystal urine present, eosinophilia, hemoglobin decreased, hyperlipemia, increased/decreased electrolytes, increased/decreased cholesterol, increased glucocorticoids, increased LDH, increased/decreased/abnormal platelets, increased gastrin levels and positive fecal occult blood. Urine abnormalities such as albuminuria, glycosuria, and hematuria were also reported. Additional isolated laboratory abnormalities were reported.

In the placebo controlled studies, when SGOT (AST) and SGPT (ALT) were evaluated, 0.4% (4/978) and 0.4% (11/2677) patients, who received placebo and lansoprazole, respectively, had enzyme elevations greater than three times the upper limit of normal range at the final treatment visit. None of these patients who received lansoprazole reported jaundice at any time during the study.

In clinical trials using combination therapy with lansoprazole plus amoxicillin and clarithromycin, and lansoprazole plus amoxicillin, no increased laboratory abnormalities particular to these drug combinations were observed.

For information on laboratory value changes with amoxicillin or clarithromycin, refer to their full prescribing information, ADVERSE REACTIONS sections.

7 DRUG INTERACTIONS

Drugs with pH-Dependent Absorption Kinetics

Lansoprazole causes long-lasting inhibition of gastric acid secretion. Lansoprazole and other PPIs are likely to substantially decrease the systemic concentrations of the HIV protease inhibitor atazanavir, which is dependent upon the presence of gastric acid for absorption, and may result in a loss of therapeutic effect of atazanavir and the development of HIV resistance. Therefore, lansoprazole and other PPIs should not be co-administered with atazanavir. [See Clinical Pharmacology (12.5)]

It is theoretically possible that lansoprazole and other PPIs may interfere with the absorption of other drugs where gastric pH is an important determinant of oral bioavailability (e.g., ampicillin esters, digoxin, iron salts, ketoconazole). [See Clinical Pharmacology (12.5)]

Warfarin

In a study of healthy subjects, co-administration of single or multiple 60 mg doses of lansoprazole and warfarin did not affect the pharmacokinetics of warfarin nor prothrombin time. [see Clinical Pharmacology (12.5)] However, there have been reports of increased INR and prothrombin time in patients receiving PPIs and warfarin concomitantly. Increases in INR and prothrombin time may lead to abnormal bleeding and even death. Patients treated with PPIs and warfarin concomitantly may need to be monitored for increases in INR and prothrombin time. [See Clinical Pharmacology (12.5)]

Tacrolimus

Concomitant administration of lansoprazole and tacrolimus may increase whole blood levels of tacrolimus, especially in transplant patients who are intermediate or poor metabolizers of CYP2C19.

Theophylline

A minor increase (10%) in the clearance of theophylline was observed following the administration of lansoprazole concomitantly with theophylline. Although the magnitude of the effect on theophylline clearance is small, individual patients may require additional titration of their theophylline dosage when lansoprazole is started or stopped to ensure clinically effective blood levels. [See Clinical Pharmacology (12.5)]

For information on drug interactions for amoxicillin or clarithromycin, refer to their full prescribing information, DRUG INTERACTIONS sections.

8 USE IN SPECIFIC POPULATIONS

8.1 Pregnancy

Teratogenic effects

Pregnancy Category B. Reproduction studies have been performed in pregnant rats at oral lansoprazole doses up to 150 mg/kg/day [49 times the recommended human dose (30 mg/day) based on body surface area (BSA)] and pregnant rabbits at oral lansoprazole doses up to 30 mg/kg/day (19 times the recommended human dose based on BSA) and have revealed no evidence of impaired fertility or harm to the fetus due to lansoprazole. There are, however, no adequate or well-controlled studies in pregnant women. Because animal reproduction studies are not always predictive of human response, this drug should be used during pregnancy only if clearly needed.

See full prescribing information for clarithromycin before using in pregnant women.

8.3 Nursing Mothers

Lansoprazole or its metabolites are excreted in the milk of rats. It is not known whether lansoprazole is excreted in human milk. Because many drugs are excreted in human milk, because of the potential for serious adverse reactions in nursing infants from lansoprazole, and because of the potential for tumorigenicity shown for lansoprazole in rat carcinogenicity studies, a decision should be made whether to discontinue nursing or to discontinue lansoprazole, taking into account the importance of lansoprazole to the mother.

8.4 Pediatric Use

The safety and effectiveness of lansoprazole have been established in pediatric patients 1 to 17 years of age for short-term treatment of symptomatic GERD and erosive esophagitis, however, lansoprazole was not effective in patients with symptomatic GERD 1 month to less than 1 year of age in a multi-center, double-blind, placebo controlled study

Neonate to less than 1 year of age

The pharmacokinetics of lansoprazole were studied in pediatric patients with GERD aged less than 28 days and 1 to 11 months. Compared to healthy adults receiving 30 mg, neonates had higher exposure (mean weight-based normalized AUC values 2.04- and 1.88-fold higher at doses of 0.5 mg/kg/day and 1 mg/kg/day, respectively). Infants aged ≤ 10 weeks had clearance and exposure values that were similar to neonates. Infants aged greater than 10 weeks who received 1 mg/kg/day had mean AUC values that were similar to adults who received a 30 mg dose.

Lansoprazole was not found to be effective in a U.S. and Polish 4 week multicenter, double-blind, placebo-controlled, parallel-group study of 162 patients between one month and less than 12 months of age with symptomatic GERD based on a medical history of crying/fussing/irritability associated with feedings who had not responded to conservative GERD management (i.e., non-pharmacologic intervention) for 7 to 14 days. Patients received lansoprazole as a suspension daily (0.2 to 0.3 mg/kg/day in infants ≤ 10 weeks of age or 1 to 1.5 mg/kg/day in infants greater than 10 weeks or placebo) for up to 4 weeks of double-blind treatment.

The primary efficacy endpoint was assessed by greater than 50% reduction from baseline in either the percent of feedings with a crying/fussing/irritability episode or the duration (minutes) of a crying/fussing/irritability episode within one hour after feeding.

There was no difference in the percentage of responders between the lansoprazole pediatric suspension group and placebo group (54% in both groups).

There were no adverse events reported in pediatric clinical studies (1 month to less than 12 months of age) that were not previously observed in adults.

Based on the results of the Phase 3 efficacy study, lansoprazole was not shown to be effective. Therefore, these results do not support the use of lansoprazole in treating symptomatic GERD in infants.

One to 11 years of age

In an uncontrolled, open-label, U.S. multicenter study, 66 pediatric patients (1 to 11 years of age) with GERD were assigned, based on body weight, to receive an initial dose of either lansoprazole 15 mg daily if < 30 kg or lansoprazole 30 mg daily if greater than 30 kg administered for 8 to 12 weeks. The lansoprazole dose was increased (up to 30 mg twice daily) in 24 of 66 pediatric patients after 2 or more weeks of treatment if they remained symptomatic. At baseline 85% of patients had mild to moderate overall GERD symptoms (assessed by investigator interview), 58% had non-erosive GERD and 42% had erosive esophagitis (assessed by endoscopy).

After 8 to 12 weeks of lansoprazole treatment, the intent-to-treat analysis demonstrated an approximate 50% reduction in frequency and severity of GERD symptoms.

Twenty-one of 27 erosive esophagitis patients were healed at 8 weeks and 100% of patients were healed at 12 weeks by endoscopy (Table 2).

Table 2: GERD Symptom Improvement and Erosive Esophagitis Healing Rates in Pediatric Patients Age 1 to 11
GERD | Final Visit [At Week 8 or Week 12] % (n/N)
Symptomatic GERD Improvement in Overall GERD Symptoms [Symptoms assessed by patients diary kept by caregiver.] | 76% (47/62 [No data were available for 4 pediatric patients.])
Erosive Esophagitis Improvement in Overall GERD Symptoms Healing Rate | 81% (22/27) 100% (27/27)

In a study of 66 pediatric patients in the age group 1 year to 11 years old after treatment with lansoprazole given orally in doses of 15 mg daily to 30 mg twice daily, increases in serum gastrin levels were similar to those observed in adult studies. Median fasting serum gastrin levels increased 89% from 51 pg/mL at baseline to 97 pg/mL [interquartile range (25th to 75th percentile) of 71 to 130 pg/mL] at the final visit.

The pediatric safety of lansoprazole delayed-release capsules has been assessed in 66 pediatric patients aged 1 to 11 years of age. Of the 66 patients with GERD 85% (56/66) took lansoprazole for 8 weeks and 15% (10/66) took it for 12 weeks.

The most frequently reported (2 or more patients) treatment-related adverse reactions in patients 1 to 11 years of age (N=66) were constipation (5%) and headache (3%).

Twelve to 17 years of age

In an uncontrolled, open-label, U.S. multicenter study, 87 adolescent patients (12 to 17 years of age) with symptomatic GERD were treated with lansoprazole for 8 to 12 weeks. Baseline upper endoscopies classified these patients into two groups: 64 (74%) nonerosive GERD and 23 (26%) erosive esophagitis (EE). The nonerosive GERD patients received lansoprazole 15 mg daily for 8 weeks and the EE patients received lansoprazole 30 mg daily for 8 to 12 weeks. At baseline, 89% of these patients had mild to moderate overall GERD symptoms (assessed by investigator interviews). During 8 weeks of lansoprazole treatment, adolescent patients experienced a 63% reduction in frequency and a 69% reduction in severity of GERD symptoms based on diary results.

Twenty-one of 22 (95.5%) adolescent erosive esophagitis patients were healed after 8 weeks of lansoprazole treatment. One patient remained unhealed after 12 weeks of treatment (Table 3).

Table 3: GERD Symptom Improvement and Erosive Esophagitis Healing Rates in Pediatric Patients Age 12 to 17
GERD | Final Visit % (n/N)
Symptomatic GERD (All Patients) Improvement in Overall GERD Symptoms [Symptoms assessed by patient diary (parents/caregivers as necessary).] | 73.2% (60/82) [No data available for 5 patients.]
Nonerosive GERD Improvement in Overall GERD Symptoms | 71.2% (42/59)
Erosive Esophagitis Improvement in Overall GERD Symptoms Healing Rate [Data from one healed patient was excluded from this analysis due to timing of final endoscopy.] | 78.3% (18/23) 95.5% (21/22)

In these 87 adolescent patients, increases in serum gastrin levels were similar to those observed in adult studies, median fasting serum gastrin levels increased 42% from 45 pg/mL at baseline to 64 pg/mL [interquartile range (25th to 75th percentile) of 44 to 88 pg/mL] at the final visit. (Normal serum gastrin levels are 25 to 111 pg/mL).

The safety of lansoprazole delayed-release capsules has been assessed in these 87 adolescent patients. Of the 87 adolescent patients with GERD, 6% (5/87) took lansoprazole for less than 6 weeks, 93% (81/87) for 6 to 10 weeks, and 1% (1/87) for greater than 10 weeks.

The most frequently reported (at least 3%) treatment-related adverse reactions in these patients were headache (7%), abdominal pain (5%), nausea (3%) and dizziness (3%). Treatment-related dizziness, reported in this package insert as occurring in less than 1% of adult patients, was reported in this study by 3 adolescent patients with nonerosive GERD, who had dizziness concurrently with other reactions (such as migraine, dyspnea, and vomiting).

8.5 Geriatric Use

No dosage adjustment of lansoprazole is necessary in geriatric patients. The incidence rates of lansoprazole-associated adverse reactions and laboratory test abnormalities are similar to those seen in younger patients. [See Clinical Pharmacology (12.4)]

8.6 Renal Impairment

No dosage adjustment of lansoprazole is necessary in patients with renal impairment. The pharmacokinetics of lansoprazole in patients with various degrees of renal impairment were not substantially different compared to those in subjects with normal renal function. [See Clinical Pharmacology (12.4)]

8.7 Hepatic Impairment

In patients with various degrees of chronic hepatic impairment, an increase in the mean AUC of up to 500% was observed at steady state compared to healthy subjects. Consider dose reduction in patients with severe hepatic impairment. [See Clinical Pharmacology (12.4)]

8.8 Gender

Over 4,000 women were treated with lansoprazole. Ulcer healing rates in females were similar to those in males. The incidence rates of adverse reactions in females were similar to those seen in males. [See Clinical Pharmacology (12.4)]

8.9 Race

The pooled mean pharmacokinetic parameters of lansoprazole from twelve U.S. Phase 1 studies (N=513) were compared to the mean pharmacokinetic parameters from two Asian studies (N=20). The mean AUCs of lansoprazole in Asian subjects were approximately twice those seen in pooled U.S. data; however, the inter-individual variability was high. The Cmax values were comparable.

10 OVERDOSAGE

Lansoprazole is not removed from the circulation by hemodialysis. In one reported overdose, a patient consumed 600 mg of lansoprazole with no adverse reaction. Oral lansoprazole doses up to 5000 mg/kg in rats (approximately 1600 times the 30 mg human dose based on BSA) and in mice (about 800 times the 30 mg human dose based on BSA) did not produce deaths or any clinical signs.

11 DESCRIPTION

The active ingredient in Lansoprazole Delayed-Release Capsules is lansoprazole, a substituted benzimidazole, 2-[[[3-methyl-4-(2,2,2-trifluoroethoxy)-2-pyridyl] methyl] sulfinyl] benzimidazole, a compound that inhibits gastric acid secretion. Its empirical formula is C16H14F3N3O2S with a molecular weight of 369.37. Lansoprazole has the following structure:

Lansoprazole is a white to brownish-white odorless crystalline powder which melts with decomposition at approximately 166°C. Lansoprazole is freely soluble in dimethylformamide; soluble in methanol; sparingly soluble in ethanol; slightly soluble in ethyl acetate, dichloromethane and acetonitrile; very slightly soluble in ether; and practically insoluble in hexane and water.

Lansoprazole is stable when exposed to light for up to two months. The rate of degradation of the compound in aqueous solution increases with decreasing pH. The degradation half-life of the drug substance in aqueous solution at 25°C is approximately 0.5 hour at pH 5.0 and approximately 18 hours at pH 7.0.

Lansoprazole is supplied in delayed-release capsules for oral administration.

Lansoprazole delayed-release capsules are available in two dosage strengths: 15 mg and 30 mg of lansoprazole per capsule. Each delayed-release capsule contains enteric-coated granules consisting of 15 mg or 30 mg of lansoprazole (active ingredient) and the following inactive ingredients: sugar sphere, sucrose, methacrylic acid copolymer, low substituted hydroxypropyl cellulose, starch, magnesium carbonate, talc, polyethylene glycol, titanium dioxide, polysorbate 80, hydroxypropyl cellulose, colloidal silicon dioxide, D&C Red No. 28, FD&C Blue No. 1, FD&C Green No. 3 [Lansoprazole 15-mg capsules only.] , and FD&C Red No. 40.

12 CLINICAL PHARMACOLOGY

12.1 Mechanism of Action

Lansoprazole belongs to a class of antisecretory compounds, the substituted benzimidazoles, that suppress gastric acid secretion by specific inhibition of the (H^+, K^+)-ATPase enzyme system at the secretory surface of the gastric parietal cell. Because this enzyme system is regarded as the acid (proton) pump within the parietal cell, lansoprazole has been characterized as a gastric acid-pump inhibitor, in that it blocks the final step of acid production. This effect is dose-related and leads to inhibition of both basal and stimulated gastric acid secretion irrespective of the stimulus. Lansoprazole does not exhibit anticholinergic or histamine type-2 antagonist activity.

12.2 Pharmacodynamics

Antisecretory Activity: After oral administration, lansoprazole was shown to significantly decrease the basal acid output and significantly increase the mean gastric pH and percent of time the gastric pH was greater than 3 and greater than 4. Lansoprazole also significantly reduced meal-stimulated gastric acid output and secretion volume, as well as pentagastrin-stimulated acid output. In patients with hypersecretion of acid, lansoprazole significantly reduced basal and pentagastrin-stimulated gastric acid secretion. Lansoprazole inhibited the normal increases in secretion volume, acidity and acid output induced by insulin.

The intragastric pH results of a five-day, pharmacodynamic, crossover study of 15 mg and 30 mg of once daily lansoprazole are presented in Table 4:

Table 4: Mean Antisecretory Effects After Single and Multiple Daily Lansoprazole Dosing
 |  | Lansoprazole
Parameter | Baseline Value | 15 mg |  | 30 mg
Parameter | Baseline Value | Day 1 | Day 5 | Day 1 | Day 5
Mean 24-Hour pH | 2.1 | 2.7 [(p<0.05) versus baseline only.] | 4 | 3.6 [(p<0.05) versus baseline and lansoprazole 15 mg.] | 4.9
Mean Nighttime pH | 1.9 | 2.4 | 3 | 2.6 | 3.8
% Time Gastric pH>3 | 18 | 33 | 59 | 51 | 72
% Time Gastric pH>4 | 12 | 22 | 49 | 41 | 66
NOTE: An intragastric pH of greater than 4 reflects a reduction in gastric acid by 99%.

After the initial dose in this study, increased gastric pH was seen within 1 to 2 hours with 30 mg of lansoprazole and 2 to 3 hours with 15 mg of lansoprazole. After multiple daily dosing, increased gastric pH was seen within the first hour post-dosing with 30 mg of lansoprazole and within 1 to 2 hours post-dosing with 15 mg of lansoprazole.

Acid suppression may enhance the effect of antimicrobials in eradicating Helicobacter pylori (H. pylori). The percentage of time gastric pH was elevated above 5 and 6 was evaluated in a crossover study of lansoprazole given daily, twice daily and three times daily (Table 5).

Table 5: Mean Antisecretory Effects After 5 Days of Twice Daily and Three Times Daily Dosing
 | Lansoprazole
Parameter | 30 mg daily | 15 mg twice daily | 30 mg twice daily | 30 mg three times daily
% Time Gastric pH>5 | 43 | 47 | 59 [(p<0.05) versus lansoprazole 30 mg daily] | 77 [(p<0.05) versus lansoprazole 30 mg daily, 15 mg twice daily and 30 mg twice daily.]
% Time Gastric pH>6 | 20 | 23 | 28 | 45

The inhibition of gastric acid secretion as measured by intragastric pH gradually returned to normal over two to four days after multiple doses. There was no indication of rebound gastric acidity.

Enterochromaffin-like (ECL) Cell Effects

During lifetime exposure of rats with up to 150 mg/kg/day of lansoprazole dosed seven days per week, marked hypergastrinemia was observed followed by ECL cell proliferation and formation of carcinoid tumors, especially in female rats. Gastric biopsy specimens from the body of the stomach from approximately 150 patients treated continuously with lansoprazole for at least one year did not show evidence of ECL cell effects similar to those seen in rat studies. Longer term data are needed to rule out the possibility of an increased risk of the development of gastric tumors in patients receiving long-term therapy with lansoprazole. [See Nonclinical Toxicology (13.1)]

Other Gastric Effects in Humans

Lansoprazole did not significantly affect mucosal blood flow in the fundus of the stomach. Due to the normal physiologic effect caused by the inhibition of gastric acid secretion, a decrease of about 17% in blood flow in the antrum, pylorus, and duodenal bulb was seen. Lansoprazole significantly slowed the gastric emptying of digestible solids. Lansoprazole increased serum pepsinogen levels and decreased pepsin activity under basal conditions and in response to meal stimulation or insulin injection. As with other agents that elevate intragastric pH, increases in gastric pH were associated with increases in nitrate-reducing bacteria and elevation of nitrite concentration in gastric juice in patients with gastric ulcer. No significant increase in nitrosamine concentrations was observed.

Serum Gastrin Effects

In over 2100 patients, median fasting serum gastrin levels increased 50% to 100% from baseline but remained within normal range after treatment with 15 to 60 mg of oral lansoprazole. These elevations reached a plateau within two months of therapy and returned to pretreatment levels within four weeks after discontinuation of therapy.

Endocrine Effects

Human studies for up to one year have not detected any clinically significant effects on the endocrine system. Hormones studied include testosterone, luteinizing hormone (LH), follicle stimulating hormone (FSH), sex hormone binding globulin (SHBG), dehydroepiandrosterone sulfate (DHEA-S), prolactin, cortisol, estradiol, insulin, aldosterone, parathormone, glucagon, thyroid stimulating hormone (TSH), triiodothyronine (T3), thyroxine (T4), and somatotropic hormone (STH). Lansoprazole in oral doses of 15 to 60 mg for up to one year had no clinically significant effect on sexual function. In addition, lansoprazole in oral doses of 15 to 60 mg for two to eight weeks had no clinically significant effect on thyroid function. In 24-month carcinogenicity studies in Sprague-Dawley rats with daily lansoprazole dosages up to 150 mg/kg, proliferative changes in the Leydig cells of the testes, including benign neoplasm, were increased compared to control rats.

Other Effects

No systemic effects of lansoprazole on the central nervous system, lymphoid, hematopoietic, renal, hepatic, cardiovascular, or respiratory systems have been found in humans. Among 56 patients who had extensive baseline eye evaluations, no visual toxicity was observed after lansoprazole treatment (up to 180 mg/day) for up to 58 months. After lifetime lansoprazole exposure in rats, focal pancreatic atrophy, diffuse lymphoid hyperplasia in the thymus, and spontaneous retinal atrophy were seen.

Microbiology

Lansoprazole, clarithromycin and/or amoxicillin have been shown to be active against most strains of Helicobacter pylori in vitro and in clinical infections as described in the INDICATIONS AND USAGE section. [See Indications and Usage (1.2)]

Helicobacter pylori Pretreatment Resistance

Clarithromycin pretreatment resistance (≥2 mcg/mL) was 9.5% (91/960) by E-test and 11.3% (12/106) by agar dilution in the dual and triple therapy clinical trials (M93-125, M93-130, M93-131, M95-392, and M95-399).

Amoxicillin pretreatment susceptible isolates (≤0.25 mcg/mL) occurred in 97.8% (936/957) and 98% (98/100) of the patients in the dual and triple therapy clinical trials by E-test and agar dilution, respectively. Twenty-one of 957 patients (2.2%) by E-test and 2 of 100 patients (2 %) by agar dilution had amoxicillin pretreatment MICs of greater than 0.25 mcg/mL. One patient on the 14-day triple therapy regimen had an unconfirmed pretreatment amoxicillin minimum inhibitory concentration (MIC) of greater than 256 mcg/mL by E-test and the patient was eradicated of H. pylori (Table 6).

Table 6: Clarithromycin Susceptibility Test Results and Clinical/Bacteriological Outcomes [Includes only patients with pretreatment clarithromycin susceptibility test results]
Clarithromycin Pretreatment Results |  | Clarithromycin Post-treatment Results
 |  | H. pylori negative – eradicated | H. pylori positive – not eradicated
 |  |  | Post-treatment susceptibility results
 |  |  | S [Susceptible (S) MIC ≤0.25 mcg/mL, Intermediate (I) MIC 0.5 to 1 mcg/mL, Resistant (R) MIC ≥2 mcg/mL] | I | R | No MIC
Triple Therapy 14-Day (lansoprazole 30 mg twice daily/amoxicillin 1 g twice daily/clarithromycin 500 mg twice daily)
(M95-399, M93-131, M95-392)
Susceptible | 112 | 105 |  |  |  | 7
Intermediate | 3 | 3
Resistant | 17 | 6 |  |  | 7 | 4
Triple Therapy 10-Day (lansoprazole 30 mg twice daily/amoxicillin 1 g twice daily/clarithromycin 500 mg twice daily)
(M95-399)
Susceptible | 42 | 40 | 1 |  | 1
Intermediate
Resistant | 4 | 1 |  |  | 3

Patients not eradicated of H. pylori following lansoprazole/amoxicillin/clarithromycin triple therapy will likely have clarithromycin resistant H. pylori. Therefore, for those patients who fail therapy, clarithromycin susceptibility testing should be done when possible. Patients with clarithromycin resistant H. pylori should not be treated with lansoprazole/amoxicillin/clarithromycin triple therapy or with regimens which include clarithromycin as the sole antimicrobial agent.

Amoxicillin Susceptibility Test Results and Clinical/Bacteriological Outcomes: In the dual and triple therapy clinical trials, 82.6% (195/236) of the patients that had pretreatment amoxicillin susceptible MICs (≤0.25 mcg/mL) were eradicated of H. pylori. Of those with pretreatment amoxicillin MICs of greater than 0.25 mcg/mL, three of six had the H. pylori eradicated. A total of 30% (21/70) of the patients failed lansoprazole 30 mg three times daily/amoxicillin 1 gm three times daily dual therapy and a total of 12.8% (22/172) of the patients failed the 10- and 14-day triple therapy regimens. Post-treatment susceptibility results were not obtained on 11 of the patients who failed therapy. Nine of the 11 patients with amoxicillin post-treatment MICs that failed the triple therapy regimen also had clarithromycin resistant H. pylori isolates.

Susceptibility Test for Helicobacter pylori: The reference methodology for susceptibility testing of H. pylori is agar dilution MICs.^1 One to three microliters of an inoculum equivalent to a No. 2 McFarland standard (1 × 10^7 to 1 × 10^8 CFU/mL for H. pylori) are inoculated directly onto freshly prepared antimicrobial-containing Mueller-Hinton agar plates with 5% aged defibrinated sheep blood (≥ 2 weeks old). The agar dilution plates are incubated at 35°C in a microaerobic environment produced by a gas generating system suitable for campylobacters.

After 3 days of incubation, the MICs are recorded as the lowest concentration of antimicrobial agent required to inhibit growth of the organism. The clarithromycin and amoxicillin MIC values should be interpreted according to the following criteria (Table 7):

Table 7
Clarithromycin MIC (mcg/mL) [These are tentative breakpoints for the agar dilution methodology and they should not be used to interpret results obtained using alternative methods.] | Interpretation
≤0.25 | Susceptible (S)
0.5 - 1 | Intermediate (I)
≥2 | Resistant (R)
Amoxicillin MIC (mcg/mL) [There were not enough organisms with MICs greater than 0.25 mcg/mL to determine a resistance breakpoint.] | Interpretation
≤0.25 | Susceptible (S)

Standardized susceptibility test procedures require the use of laboratory control microorganisms to control the technical aspects of the laboratory procedures. Standard clarithromycin and amoxicillin powders should provide the following MIC values (Table 8):

Table 8
Microorganism | Antimicrobial Agent | MIC (mcg/mL) [These are quality control ranges for the agar dilution methodology and they should not be used to control test results obtained using alternative methods.]
H. pylori ATCC 43504 | Clarithromycin | 0.015 - 0.12
H. pylori ATCC 43504 | Amoxicillin | 0.015 - 0.12

12.3 Pharmacokinetics

Lansoprazole delayed-release capsules contain an enteric-coated granule formulation of lansoprazole. Absorption of lansoprazole begins only after the granules leave the stomach. Absorption is rapid, with mean peak plasma levels of lansoprazole occurring after approximately 1.7 hours. After a single-dose administration of 15 mg to 60 mg of oral lansoprazole, the peak plasma concentrations (Cmax) of lansoprazole and the area under the plasma concentration curves (AUCs) of lansoprazole were approximately proportional to the administered dose. Lansoprazole does not accumulate and its pharmacokinetics are unaltered by multiple dosing.

Absorption: The absorption of lansoprazole is rapid, with the mean Cmax occurring approximately 1.7 hours after oral dosing, and the absolute bioavailability is over 80%. In healthy subjects, the mean (±SD) plasma half-life was 1.5 (±1) hours. Both the Cmax and AUC are diminished by about 50% to 70% if lansoprazole is given 30 minutes after food, compared to the fasting condition. There is no significant food effect if lansoprazole is given before meals.

Distribution: Lansoprazole is 97% bound to plasma proteins. Plasma protein binding is constant over the concentration range of 0.05 to 5 mcg/mL.

Metabolism: Lansoprazole is extensively metabolized in the liver. Two metabolites have been identified in measurable quantities in plasma (the hydroxylated sulfinyl and sulfone derivatives of lansoprazole). These metabolites have very little or no antisecretory activity. Lansoprazole is thought to be transformed into two active species which inhibit acid secretion by blocking the proton pump [(H^+, K^+)-ATPase enzyme system] at the secretory surface of the gastric parietal cell. The two active species are not present in the systemic circulation. The plasma elimination half-life of lansoprazole is less than 2 hours while the acid inhibitory effect lasts more than 24 hours. Therefore, the plasma elimination half-life of lansoprazole does not reflect its duration of suppression of gastric acid secretion.

Elimination: Following single-dose oral administration of lansoprazole, virtually no unchanged lansoprazole was excreted in the urine. In one study, after a single oral dose of ^14C-lansoprazole, approximately one-third of the administered radiation was excreted in the urine and two-thirds was recovered in the feces. This implies a significant biliary excretion of the lansoprazole metabolites.

12.4 Specific Populations

Pediatric Use:

One to 17 years of age

The pharmacokinetics of lansoprazole were studied in pediatric patients with GERD aged 1 to 11 years and 12 to 17 years in two separate clinical studies. In children aged 1 to 11 years, lansoprazole was dosed 15 mg daily for subjects weighing ≤ 30 kg and 30 mg daily for subjects weighing greater than 30 kg. Mean Cmax and AUC values observed on Day 5 of dosing were similar between the two dose groups and were not affected by weight or age within each weight-adjusted dose group used in the study. In adolescent subjects aged 12 to 17 years, subjects were randomized to receive lansoprazole at 15 mg or 30 mg daily. Mean Cmax and AUC values of lansoprazole were not affected by body weight or age; and nearly dose-proportional increases in mean Cmax and AUC values were observed between the two dose groups in the study. Overall, lansoprazole pharmacokinetics in pediatric patients aged 1 to 17 years were similar to those observed in healthy adult subjects.

Neonate to less than one year of age

Refer to Section 8.4 for the pharmacokinetics of lansoprazole in pediatric patients with GERD aged less than 28 days and 1 to 11 months.

Geriatric Use: The clearance of lansoprazole is decreased in the elderly, with elimination half-life increased approximately 50% to 100%. Because the mean half-life in the elderly remains between 1.9 to 2.9 hours, repeated once daily dosing does not result in accumulation of lansoprazole. Peak plasma levels were not increased in the elderly. No dosage adjustment is necessary in the elderly [See Use in Specific Populations (8.5)].

Renal Impairment: In patients with severe renal impairment, plasma protein binding decreased by 1% to 1.5% after administration of 60 mg of lansoprazole. Patients with renal impairment had a shortened elimination half-life and decreased total AUC (free and bound). The AUC for free lansoprazole in plasma, however, was not related to the degree of renal impairment; and the Cmax and tmax (time to reach the maximum concentration) were not different than the Cmax and tmax from subjects with normal renal function. No dosage adjustment is necessary in patients with renal impairment [See Use in Specific Populations (8.6].

Hepatic Impairment: In patients with various degrees of chronic hepatic impairment, the mean plasma half-life of lansoprazole was prolonged from 1.5 hours to 3.2 to 7.2 hours. An increase in the mean AUC of up to 500% was observed at steady state in hepatically-impaired patients compared to healthy subjects. Consider dose reduction in patients with severe hepatic impairment [See Use in Specific Populations (8.7)].

Gender: In a study comparing 12 male and 6 female human subjects who received lansoprazole, no gender differences were found in pharmacokinetics and intragastric pH results [See Use in Specific Populations (8.5)].

12.5 Drug-Drug Interactions

It is theoretically possible that lansoprazole may interfere with the absorption of other drugs where gastric pH is an important determinant of bioavailability (e.g., ketoconazole, ampicillin esters, iron salts, digoxin).

Lansoprazole is metabolized through the cytochrome P450 system, specifically through the CYP3A and CYP2C19 isozymes. Studies have shown that lansoprazole does not have clinically significant interactions with other drugs metabolized by the cytochrome P450 system, such as warfarin, antipyrine, indomethacin, ibuprofen, phenytoin, propranolol, prednisone, diazepam, or clarithromycin in healthy subjects. These compounds are metabolized through various cytochrome P450 isozymes including CYP1A2, CYP2C9, CYP2C19, CYP2D6, and CYP3A.

Atazanavir: lansoprazole causes long-lasting inhibition of gastric acid secretion. Lansoprazole substantially decreases the systemic concentrations of the HIV protease inhibitor atazanavir, which is dependent upon the presence of gastric acid for absorption, and may result in a loss of therapeutic effect of atazanavir and the development of HIV resistance. Therefore, lansoprazole, or other proton pump inhibitors, should not be co-administered with atazanavir.

Theophylline: When lansoprazole was administered concomitantly with theophylline (CYP1A2, CYP3A), a minor increase (10%) in the clearance of theophylline was seen. Because of the small magnitude and the direction of the effect on theophylline clearance, this interaction is unlikely to be of clinical concern. Nonetheless, individual patients may require additional titration of their theophylline dosage when lansoprazole is started or stopped to ensure clinically effective blood levels.

Warfarin: In a study of healthy subjects neither the pharmacokinetics of warfarin enantiomers nor prothrombin time were affected following single or multiple 60 mg doses of lansoprazole. However, there have been reports of increased International Normalized Ratio (INR) and prothrombin time in patients receiving proton pump inhibitors, including lansoprazole, and warfarin concomitantly. Increases in INR and prothrombin time may lead to abnormal bleeding and even death. Patients treated with proton pump inhibitors and warfarin concomitantly may need to be monitored for increases in INR and prothrombin time.

Methotrexate and 7-hydromethotrexate: In an open-label, single-arm, eight-day, pharmacokinetic study of 28 adult rheumatoid arthritis patients (who required the chronic use of 7.5 to 15 mg of methotrexate given weekly), administration of 7 days of naproxen 500 mg twice daily and lansoprazole 30 mg daily had no effect on the pharmacokinetics of methotrexate and 7-hydroxymethotrexate. While this study was not designed to assess the safety of this combination of drugs, no major adverse reactions were noted.

Amoxicillin: Lansoprazole has also been shown to have no clinically significant interaction with amoxicillin.

Sucralfate: In a single-dose crossover study examining lansoprazole 30 mg and omeprazole 20 mg each administered alone and concomitantly with sucralfate 1 gram, absorption of the proton pump inhibitors was delayed and their bioavailability was reduced by 17% and 16%, respectively, when administered concomitantly with sucralfate. Therefore, proton pump inhibitors should be taken at least 30 minutes prior to sucralfate. In clinical trials, antacids were administered concomitantly with lansoprazole and there was no evidence of a change in the efficacy of lansoprazole.

13 NONCLINICAL TOXICOLOGY

13.1 Carcinogenesis, Mutagenesis, Impairment of Fertility

In two 24-month carcinogenicity studies, Sprague-Dawley rats were treated with oral lansoprazole doses of 5 to 150 mg/kg/day, about 1 to 40 times the exposure on a body surface (mg/m^2) basis of a 50 kg person of average height (1.46 m^2 BSA) given the recommended human dose of lansoprazole (30 mg/day) . Lansoprazole produced dose-related gastric enterochromaffin-like (ECL) cell hyperplasia and ECL cell carcinoids in both male and female rats. It also increased the incidence of intestinal metaplasia of the gastric epithelium in both sexes. In male rats, lansoprazole produced a dose-related increase of testicular interstitial cell adenomas. The incidence of these adenomas in rats receiving doses of 15 to 150 mg/kg/day (4 to 40 times the recommended human dose based on BSA) exceeded the low background incidence (range = 1.4 to 10%) for this strain of rat. In addition, in a one-year toxicity study, testicular interstitial cell adenoma occurred in 1 of 30 rats treated with 50 mg/kg/day of lansoprazole (13 times the recommended human dose based on BSA).

In a 24-month carcinogenicity study, CD-1 mice were treated with oral lansoprazole doses of 15 to 600 mg/kg/day, 2 to 80 times the recommended human dose based on BSA. Lansoprazole produced a dose-related increased incidence of gastric ECL cell hyperplasia. It also produced an increased incidence of liver tumors (hepatocellular adenoma plus carcinoma). The tumor incidences in male mice treated with 300 and 600 mg/kg/day (40 to 80 times the recommended human dose based on BSA) and female mice treated with 150 to 600 mg/kg/day (20 to 80 times the recommended human dose based on BSA) exceeded the ranges of background incidences in historical controls for this strain of mice. Lansoprazole treatment produced adenoma of rete testis in male mice receiving 75 to 600 mg/kg/day (10 to 80 times the recommended human dose based on BSA).

A 26-week p53 (+/-) transgenic mouse carcinogenicity study was not positive.

Lansoprazole was not genotoxic in the Ames test, the ex vivo rat hepatocyte unscheduled DNA synthesis (UDS) test, the in vivo mouse micronucleus test, or the rat bone marrow cell chromosomal aberration test. It was positive in in vitro human lymphocyte chromosomal aberration assays.

Lansoprazole at oral doses up to 150 mg/kg/day (40 times the recommended human dose based on BSA) was found to have no effect on fertility and reproductive performance of male and female rats.

14 CLINICAL STUDIES

Duodenal Ulcer

In a U.S. multicenter, double-blind, placebo-controlled, dose-response (15, 30, and 60 mg of lansoprazole once daily) study of 284 patients with endoscopically documented duodenal ulcer, the percentage of patients healed after two and four weeks was significantly higher with all doses of lansoprazole than with placebo. There was no evidence of a greater or earlier response with the two higher doses compared with lansoprazole 15 mg. Based on this study and the second study described below, the recommended dose of lansoprazole in duodenal ulcer is 15 mg per day (Table 9).

Table 9: Duodenal Ulcer Healing Rates
 | Lansoprazole |  |  | Placebo
Week | 15 mg daily | 30 mg daily | 60 mg daily | Placebo
Week | (N=68) | (N=74) | (N=70) | (N=72)
2 | 42.4% [(p≤0.001) versus placebo.] | 35.6% | 39.1% | 11.3%
4 | 89.4% | 91.7% | 89.9% | 46.1%

Lansoprazole 15 mg was significantly more effective than placebo in relieving day and nighttime abdominal pain and in decreasing the amount of antacid taken per day.

In a second U.S. multicenter study, also double-blind, placebo-controlled, dose-comparison (15 and 30 mg of lansoprazole once daily), and including a comparison with ranitidine, in 280 patients with endoscopically documented duodenal ulcer, the percentage of patients healed after four weeks was significantly higher with both doses of lansoprazole than with placebo. There was no evidence of a greater or earlier response with the higher dose of lansoprazole. Although the 15 mg dose of lansoprazole was superior to ranitidine at 4 weeks, the lack of significant difference at 2 weeks and the absence of a difference between 30 mg of lansoprazole and ranitidine leaves the comparative effectiveness of the two agents undetermined (Table 10). [See Indications and Usage (1.1)]

Table 10: Duodenal Ulcer Healing Rates
 | Lansoprazole |  | Ranitidine | Placebo
Week | 15 mg daily | 30 mg daily | 300 mg h.s. | Placebo
Week | (N=80) | (N=77) | (N=82) | (N=41)
2 | 35% | 44.2% | 30.5% | 34.2%
4 | 92.3% [(p≤0.05) versus placebo and ranitidine.] | 80.3% [(p≤0.05) versus placebo.] | 70.5% | 47.5%

H. pylori Eradication to Reduce the Risk of Duodenal Ulcer Recurrence

Randomized, double-blind clinical studies performed in the U.S. in patients with H. pylori and duodenal ulcer disease (defined as an active ulcer or history of an ulcer within one year) evaluated the efficacy of lansoprazole in combination with amoxicillin capsules and clarithromycin tablets as triple 14-day therapy or in combination with amoxicillin capsules as dual 14-day therapy for the eradication of H. pylori. Based on the results of these studies, the safety and efficacy of two different eradication regimens were established:

Triple therapy: Lansoprazole 30 mg twice daily/amoxicillin 1 g twice daily/clarithromycin 500 mg twice daily

Dual therapy: Lansoprazole 30 mg three times daily/amoxicillin 1 g three times daily

All treatments were for 14 days. H. pylori eradication was defined as two negative tests (culture and histology) at 4 to 6 weeks following the end of treatment.

Triple therapy was shown to be more effective than all possible dual therapy combinations. Dual therapy was shown to be more effective than both monotherapies. Eradication of H. pylori has been shown to reduce the risk of duodenal ulcer recurrence.

A randomized, double-blind clinical study performed in the U.S. in patients with H. pylori and duodenal ulcer disease (defined as an active ulcer or history of an ulcer within one year) compared the efficacy of lansoprazole triple therapy for 10 and 14 days. This study established that the 10-day triple therapy was equivalent to the 14-day triple therapy in eradicating H. pylori (Tables 11 and 12). [See Indications and Usage (1.2)]

Table 11 H. pylori Eradication Rates – Triple Therapy (lansoprazole/amoxicillin/clarithromycin) Percent of Patients Cured [95% Confidence Interval] (Number of patients)
Study | Duration | Triple Therapy Evaluable Analysis [Based on evaluable patients with confirmed duodenal ulcer (active or within one year) and H. pylori infection at baseline defined as at least two of three positive endoscopic tests from CLOtest®, histology and/or culture. Patients were included in the analysis if they completed the study. Additionally, if patients dropped out of the study due to an adverse event related to the study drug, they were included in the evaluable analysis as failures of therapy.] | Triple Therapy Intent-to-Treat Analysis [Patients were included in the analysis if they had documented H. pylori infection at baseline as defined above and had a confirmed duodenal ulcer (active or within one year). All dropouts were included as failures of therapy.]
M93-131 | 14 days | 92 [(p<0.05) versus lansoprazole/amoxicillin and lansoprazole/clarithromycin dual therapy.] [80 - 97.7] (N=48) | 86 [73.3 - 93.5] (N=55)
M95-392 | 14 days | 86 [(p<0.05) versus clarithromycin/amoxicillin dual therapy.] [75.7 - 93.6] (N=66) | 83 [72 - 90.8] (N=70)
M95-399 [The 95% confidence interval for the difference in eradication rates, 10-day minus 14-day is (-10.5, 8.1) in the evaluable analysis and (-9.7, 9.1) in the intent-to-treat analysis.] | 14 days | 85 [77 - 91] (N=113) | 82 [73.9 - 88.1] (N=126)
M95-399 [The 95% confidence interval for the difference in eradication rates, 10-day minus 14-day is (-10.5, 8.1) in the evaluable analysis and (-9.7, 9.1) in the intent-to-treat analysis.] | 10 days | 84 [76 - 89.8] (N=123) | 81 [73.9 - 87.6] (N=135)

Table 12 H. pylori Eradication Rates – 14-Day Dual Therapy (lansoprazole/amoxicillin) Percent of Patients Cured [95% Confidence Interval] (Number of patients)
Study | Dual Therapy Evaluable Analysis [Based on evaluable patients with confirmed duodenal ulcer (active or within one year) and H. pylori infection at baseline defined as at least two of three positive endoscopic tests from CLOtest®, histology and/or culture. Patients were included in the analysis if they completed the study. Additionally, if patients dropped out of the study due to an adverse event related to the study drug, they were included in the analysis as failures of therapy.] | Dual Therapy Intent-to-Treat Analysis [Patients were included in the analysis if they had documented H. pylori infection at baseline as defined above and had a confirmed duodenal ulcer (active or within one year). All dropouts were included as failures of therapy.]
M93-131 | 77 [(p<0.05) versus lansoprazole alone.] [62.5 - 87.2] (N=51) | 70 [56.8 - 81.2] (N=60)
M93-125 | 66 [(p<0.05) versus lansoprazole alone or amoxicillin alone.] [51.9 - 77.5] (N=58) | 61 [48.5 - 72.9] (N=67)

Long-Term Maintenance Treatment of Duodenal Ulcers

Lansoprazole has been shown to prevent the recurrence of duodenal ulcers. Two independent, double-blind, multicenter, controlled trials were conducted in patients with endoscopically confirmed healed duodenal ulcers. Patients remained healed significantly longer and the number of recurrences of duodenal ulcers was significantly less in patients treated with lansoprazole than in patients treated with placebo over a 12-month period (Table 13). [See Indications and Usage (1.3)]

Table 13: Endoscopic Remission Rates
Trial | Drug | No. of Pts. | Percent in Endoscopic Remission
Trial | Drug | No. of Pts. | 0 - 3 mo. | 0 - 6 mo. | 0 - 12 mo.
#1 | Lansoprazole 15 mg daily | 86 | 90% [(p≤0.001) versus placebo.] | 87% | 84%
#1 | Placebo | 83 | 49% | 41% | 39%
#2 | Lansoprazole 30 mg daily | 18 | 94% | 94% | 85%
#2 | Lansoprazole 15 mg daily | 15 | 87% | 79% | 70%
#2 | Placebo | 15 | 33% | 0% | 0%
%=Life Table Estimate

In trial #2, no significant difference was noted between lansoprazole 15 mg and 30 mg in maintaining remission.

Gastric Ulcer

In a U.S. multicenter, double-blind, placebo-controlled study of 253 patients with endoscopically documented gastric ulcer, the percentage of patients healed at four and eight weeks was significantly higher with lansoprazole 15 mg and 30 mg once a day than with placebo (Table 14). [See Indications and Usage (1.4)]

Table 14: Gastric Ulcer Healing Rates
 | Lansoprazole |  |  | Placebo
Week | 15 mg daily | 30 mg daily | 60 mg daily | Placebo
Week | (N=65) | (N=63) | (N=61) | (N=64)
4 | 64.6% [(p≤0.05) versus placebo.] | 58.1% | 53.3% | 37.5%
8 | 92.2% | 96.8% | 93.2% | 76.7%

Patients treated with any lansoprazole dose reported significantly less day and night abdominal pain along with fewer days of antacid use and fewer antacid tablets used per day than the placebo group.

Independent substantiation of the effectiveness of lansoprazole 30 mg was provided by a meta-analysis of published and unpublished data.

Healing of NSAID-Associated Gastric Ulcer

In two U.S. and Canadian multicenter, double-blind, active-controlled studies in patients with endoscopically confirmed NSAID-associated gastric ulcer who continued their NSAID use, the percentage of patients healed after 8 weeks was statistically significantly higher with 30 mg of lansoprazole than with the active control. A total of 711 patients were enrolled in the study, and 701 patients were treated. Patients ranged in age from 18 to 88 years (median age 59 years), with 67% female patients and 33% male patients. Race was distributed as follows: 87% Caucasian, 8% Black, 5% Other. There was no statistically significant difference between lansoprazole 30 mg daily and the active control on symptom relief (i.e., abdominal pain) (Table 15). [See Indications and Usage (1.5)]

Table 15: NSAID-Associated Gastric Ulcer Healing Rates [Actual observed ulcer(s) healed at time points ± 2 days]
Study #1
 | Lansoprazole | Active Control [Dose for healing of gastric ulcer]
 | 30 mg daily | Active Control [Dose for healing of gastric ulcer]
Week 4 | 60% (53/88) [(p≤0.05) versus the active control] | 28% (23/83)
Week 8 | 79% (62/79) | 55% (41/74)
Study #2
 | Lansoprazole | Active Control
 | 30 mg daily | Active Control
Week 4 | 53% (40/75) | 38% (31/82)
Week 8 | 77% (47/61) | 50% (33/66)

Risk Reduction of NSAID-Associated Gastric Ulcer

In one large U.S., multicenter, double-blind, placebo- and misoprostol-controlled (misoprostol blinded only to the endoscopist) study in patients who required chronic use of an NSAID and who had a history of an endoscopically documented gastric ulcer, the proportion of patients remaining free from gastric ulcer at 4, 8, and 12 weeks was significantly higher with 15 or 30 mg of lansoprazole than placebo. A total of 537 patients were enrolled in the study, and 535 patients were treated. Patients ranged in age from 23 to 89 years (median age 60 years), with 65% female patients and 35% male patients. Race was distributed as follows: 90% Caucasian, 6% Black, 4% other. The 30 mg dose of lansoprazole demonstrated no additional benefit in risk reduction of the NSAID-associated gastric ulcer than the 15 mg dose (Table 16). [See Indications and Usage (1.6)]

Table 16: Proportion of Patients Remaining Free of Gastric Ulcers [% = Life Table Estimate]
 | Lansoprazole | Lansoprazole | Misoprostol | Placebo
 | 15 mg daily | 30 mg daily | 200 mcg q.i.d.
Week | (N=121) | (N=116) | (N=106) | (N=112)
4 | 90% | 92% | 96% | 66%
8 | 86% | 88% | 95% | 60%
12 | 80% | 82% | 93% | 51%
(p<0.001) lansoprazole 15 mg daily versus placebo; lansoprazole 30 mg daily versus placebo; and misoprostol 200 mcg q.i.d. versus placebo.
(p<0.05) Misoprostol 200 mcg q.i.d. versus lansoprazole 15 mg daily; and misoprostol 200 mcg q.i.d. versus lansoprazole 30 mg daily.

Gastroesophageal Reflux Disease (GERD)

Symptomatic GERD: In a U.S. multicenter, double-blind, placebo-controlled study of 214 patients with frequent GERD symptoms, but no esophageal erosions by endoscopy, significantly greater relief of heartburn associated with GERD was observed with the administration of lansoprazole 15 mg once daily up to 8 weeks than with placebo. No significant additional benefit from lansoprazole 30 mg once daily was observed.

The intent-to-treat analyses demonstrated significant reduction in frequency and severity of day and night heartburn. Data for frequency and severity for the 8-week treatment period are presented in Table 17 and in Figures 1 and 2:

Table 17: Frequency of Heartburn
Variable | Placebo (n=43) | Lansoprazole 15 mg (n=80) | Lansoprazole 30 mg (n=86)
Variable | Median
% of Days without Heartburn
Week 1 | 0% | 71% [(p<0.01) versus placebo.] | 46%
Week 4 | 11% | 81% | 76%
Week 8 | 13% | 84% | 82%
% of Nights without Heartburn
Week 1 | 17% | 86% | 57%
Week 4 | 25% | 89% | 73%
Week 8 | 36% | 92% | 80%

BOXED WARNING

Figure 1

Figure 2

In two U.S., multicenter double-blind, ranitidine-controlled studies of 925 total patients with frequent GERD symptoms, but no esophageal erosions by endoscopy, lansoprazole 15 mg was superior to ranitidine 150 mg (twice daily) in decreasing the frequency and severity of day and night heartburn associated with GERD for the 8-week treatment period. No significant additional benefit from lansoprazole 30 mg once daily was observed. [See Indications and Usage (1.7)]

Erosive Esophagitis

In a U.S. multicenter, double-blind, placebo-controlled study of 269 patients entering with an endoscopic diagnosis of esophagitis with mucosal grading of 2 or more and grades 3 and 4 signifying erosive disease, the percentages of patients with healing are presented in Table 18:

Table 18: Erosive Esophagitis Healing Rates
 | Lansoprazole |  |  | Placebo
 | 15 mg daily | 30 mg daily | 60 mg daily
Week | (N=69) | (N=65) | (N=72) | (N=63)
4 | 67.6% [(p≤0.001) versus placebo.] | 81.3% [(p≤0.05) versus lansoprazole 15 mg.] | 80.6% | 32.8%
6 | 87.7% | 95.4% | 94.3% | 52.5%
8 | 90.9% | 95.4% | 94.4% | 52.5%

In this study, all lansoprazole groups reported significantly greater relief of heartburn and less day and night abdominal pain along with fewer days of antacid use and fewer antacid tablets taken per day than the placebo group.

Although all doses were effective, the earlier healing in the higher two doses suggests 30 mg daily as the recommended dose.

Lansoprazole was also compared in a U.S. multicenter, double-blind study to a low dose of ranitidine in 242 patients with erosive reflux esophagitis. Lansoprazole at a dose of 30 mg was significantly more effective than ranitidine 150 mg twice daily as shown below (Table 19).

Table 19: Erosive Esophagitis Healing Rates
Week | Lansoprazole 30 mg daily (N=115) | Ranitidine 150 mg twice daily (N=127)
2 | 66.7% [(p≤0.001) versus ranitidine.] | 38.7%
4 | 82.5% | 52%
6 | 93% | 67.8%
8 | 92.1% | 69.9%

In addition, patients treated with lansoprazole reported less day and nighttime heartburn and took less antacid tablets for fewer days than patients taking ranitidine 150 mg twice daily.

Although this study demonstrates effectiveness of lansoprazole in healing erosive esophagitis, it does not represent an adequate comparison with ranitidine because the recommended ranitidine dose for esophagitis is 150 mg q.i.d., twice the dose used in this study.

In the two trials described and in several smaller studies involving patients with moderate to severe erosive esophagitis, lansoprazole produced healing rates similar to those shown above.

In a U.S. multicenter, double-blind, active-controlled study, 30 mg of lansoprazole was compared with ranitidine 150 mg twice daily in 151 patients with erosive reflux esophagitis that was poorly responsive to a minimum of 12 weeks of treatment with at least one H2-receptor antagonist given at the dose indicated for symptom relief or greater, namely, cimetidine 800 mg/day, ranitidine 300 mg/day, famotidine 40 mg/day or nizatidine 300 mg/day. Lansoprazole 30 mg was more effective than ranitidine 150 mg twice daily in healing reflux esophagitis, and the percentage of patients with healing were as follows. This study does not constitute a comparison of the effectiveness of histamine H2-receptor antagonists with lansoprazole, as all patients had demonstrated unresponsiveness to the histamine H2-receptor antagonist mode of treatment. It does indicate, however, that lansoprazole may be useful in patients failing on a histamine H2-receptor antagonist (Table 20). [See Indications and Usage (1.7)]

Table 20: Reflux Esophagitis Healing Rates in Patients Poorly Responsive to Histamine H2-Receptor Antagonist Therapy
Week | Lansoprazole 30 mg daily (N=100) | Ranitidine 150 mg twice daily (N=51)
4 | 74.7% [(p≤0.001) versus ranitidine.] | 42.6%
8 | 83.7% | 32%

Long-Term Maintenance Treatment of Erosive Esophagitis

Two independent, double-blind, multicenter, controlled trials were conducted in patients with endoscopically confirmed healed esophagitis. Patients remained in remission significantly longer and the number of recurrences of erosive esophagitis was significantly less in patients treated with lansoprazole than in patients treated with placebo over a 12-month period (Table 21).

Table 21: Endoscopic Remission Rates
 |  |  | Percent in Endoscopic Remission
Trial | Drug | No. of Pts. | 0 - 3 mo. | 0 - 6 mo. | 0 - 12 mo.
#1 | Lansoprazole 15 mg daily | 59 | 83% [(p≤0.001) versus placebo.] | 81% | 79%
#1 | Lansoprazole 30 mg daily | 56 | 93% | 93% | 90%
#1 | Placebo | 55 | 31% | 27% | 24%
#2 | Lansoprazole 15 mg daily | 50 | 74% | 72% | 67%
#2 | Lansoprazole 30 mg daily | 49 | 75% | 72% | 55%
#2 | Placebo | 47 | 16% | 13% | 13%
%=Life Table Estimate

Regardless of initial grade of erosive esophagitis, lansoprazole 15 mg and 30 mg were similar in maintaining remission.

In a U.S., randomized, double-blind, study, lansoprazole 15 mg daily (n = 100) was compared with ranitidine 150 mg twice daily (n = 106), at the recommended dosage, in patients with endoscopically-proven healed erosive esophagitis over a 12-month period. Treatment with lansoprazole resulted in patients remaining healed (Grade 0 lesions) of erosive esophagitis for significantly longer periods of time than those treated with ranitidine (p<0.001). In addition, lansoprazole was significantly more effective than ranitidine in providing complete relief of both daytime and nighttime heartburn. Patients treated with lansoprazole remained asymptomatic for a significantly longer period of time than patients treated with ranitidine. [See Indications and Usage (1.8)]

Pathological Hypersecretory Conditions Including Zollinger-Ellison Syndrome

In open studies of 57 patients with pathological hypersecretory conditions, such as Zollinger-Ellison syndrome (ZES) with or without multiple endocrine adenomas, lansoprazole significantly inhibited gastric acid secretion and controlled associated symptoms of diarrhea, anorexia and pain. Doses ranging from 15 mg every other day to 180 mg per day maintained basal acid secretion below 10 mEq/hr in patients without prior gastric surgery and below 5 mEq/hr in patients with prior gastric surgery.

Initial doses were titrated to the individual patient need, and adjustments were necessary with time in some patients. [See Dosage and Administration (2.1)] Lansoprazole was well tolerated at these high dose levels for prolonged periods (greater than four years in some patients). In most ZES patients, serum gastrin levels were not modified by lansoprazole. However, in some patients, serum gastrin increased to levels greater than those present prior to initiation of lansoprazole therapy. [See Indications and Usage (1.9)]

15 REFERENCES

1. National Committee for Clinical Laboratory Standards. Summary Minutes, Subcommittee on Antimicrobial Susceptibility Testing, Tampa, FL, January 11-13, 1998.

16 HOW SUPPLIED/STORAGE AND HANDLING

Lansoprazole Delayed-Release Capsules, 15 mg, are opaque, hard gelatin, colored pink and green with "TAP" and "PREVACID 15" imprinted on the capsules. The 30 mg capsules are opaque, hard gelatin, colored pink and black with "TAP" and "PREVACID 30" imprinted on the capsules. They are available as follows:

NDC 21695-474-30 | Bottles of 30: 15-mg capsules
NDC 21695-652-30 | Bottles of 30: 30-mg capsules

STORAGE AND HANDLING

Store at 25°C (77°F); excursions permitted to 15-30°C (59-86°F).[See USP Controlled Room Temperature].

17 PATIENT COUNSELING INFORMATION

Patient should be informed of the following:

17.1 Information for Patients

Lansoprazole delayed-release capsules are available in 15 mg and 30 mg strengths. Directions for use specific to the route and available methods of administration is presented below. [See Dosage and Administration (2.3)]

- Lansoprazole delayed-release capsules should be taken before eating.
- Lansoprazole delayed-release capsules SHOULD NOT BE CRUSHED OR CHEWED.

Administration Options

Lansoprazole Delayed-Release Capsules

- Lansoprazole delayed-release capsules should be swallowed whole.
- Alternatively, for patients who have difficulty swallowing capsules, lansoprazole delayed-release capsules can be opened and administered as follows:
  - Open capsule.
  - Sprinkle intact granules on one tablespoon of either applesauce, ENSURE® pudding, cottage cheese, yogurt or strained pears.
  - Swallow immediately.
- Lansoprazole delayed-release capsules may also be emptied into a small volume of either apple juice, orange juice or tomato juice and administered as follows:
  - Open capsule.
  - Sprinkle intact granules into a small volume of either apple juice, orange juice or tomato juice (60 mL – approximately 2 ounces).
  - Mix briefly.
  - Swallow immediately.
  - To ensure complete delivery of the dose, the glass should be rinsed with two or more volumes of juice and the contents swallowed immediately.

USE IN OTHER FOODS AND LIQUIDS HAS NOT BEEN STUDIED CLINICALLY AND IS THEREFORE NOT RECOMMENDED.

Manufactured by:
Takeda Ireland Ltd.
Kilruddery, Co. Wicklow, Ireland
for:
Sandoz Inc.
Princeton, NJ 08540

Repackaged by:

Rebel Distributors Corp

Thousand Oaks, CA 91320

All trademark names are the property of their respective owners.

U.S. Patent Nos. - 4,628,098; 5,013,743; 5,464,632; 6,328,994
© 1995-2009 Takeda Pharmaceuticals America, Inc.

LAN0609 R1; June 2009

PRINCIPAL DISPLAY PANEL - 15 mg, 30 Capsule Label

NDC 21695-474-30

Lansoprazole
Delayed-
Release
Capsules

15 mg

Rx only

30 Capsules

SANDOZ

PRINCIPAL DISPLAY PANEL - 30 mg, 30 Capsule Label

NDC 212695-652-30

Lansoprazole
Delayed-
Release
Capsules

30 mg

Rx only

30 Capsules

SANDOZ